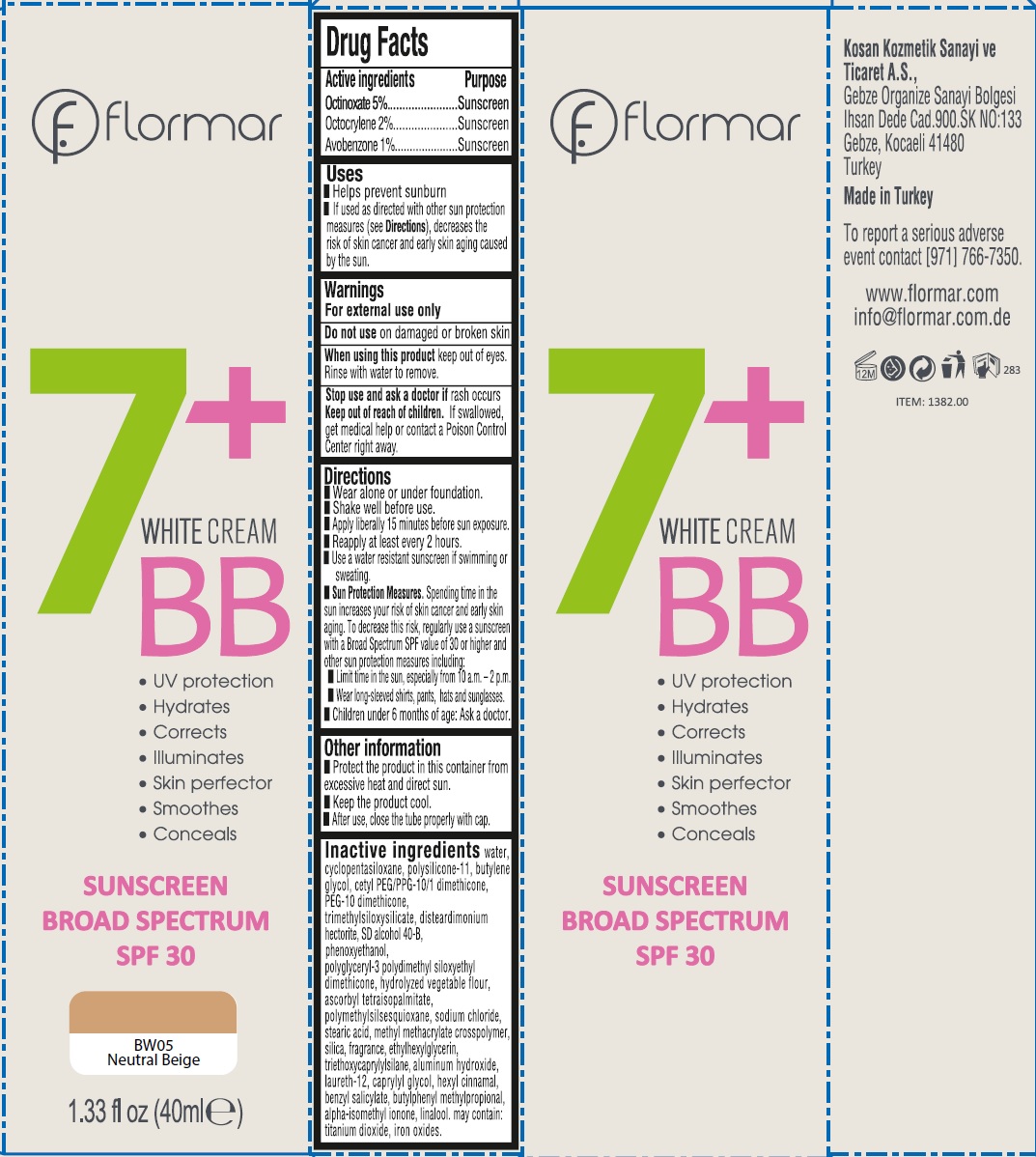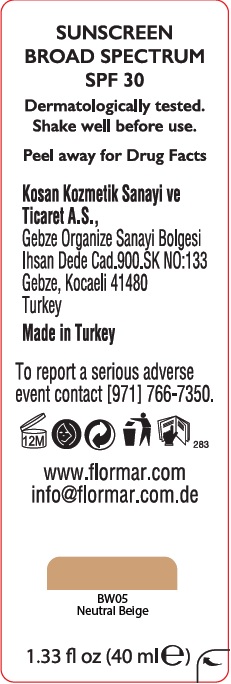 DRUG LABEL: Flormar BB White BW05 Natural Beige
NDC: 61722-294 | Form: AEROSOL
Manufacturer: Kosan Kozmetik Sanayi ve Ticaret A.S.
Category: otc | Type: HUMAN OTC DRUG LABEL
Date: 20191018

ACTIVE INGREDIENTS: OCTINOXATE 50 mg/1 mL; OCTOCRYLENE 20 mg/1 mL; AVOBENZONE 10 mg/1 mL
INACTIVE INGREDIENTS: WATER; CYCLOMETHICONE 5; DIMETHICONE/VINYL DIMETHICONE CROSSPOLYMER (SOFT PARTICLE); BUTYLENE GLYCOL; DISTEARDIMONIUM HECTORITE; PHENOXYETHANOL; ASCORBYL TETRAISOPALMITATE; SODIUM CHLORIDE; STEARIC ACID; SILICON DIOXIDE; ETHYLHEXYLGLYCERIN; TRIETHOXYCAPRYLYLSILANE; ALUMINUM HYDROXIDE; LAURETH-12; CAPRYLYL GLYCOL; BUTYLPHENYL METHYLPROPIONAL; ISOMETHYL-.ALPHA.-IONONE; LINALOOL, (+/-)-

Flormar BB White Cream BW05 Natural Beige

Active ingredients

Octinoxate 5%

Octinoxate 2%

Avobenzone 1%

Purpose

Sunscreen

Uses

- Helps prevent sunburn
- If used as directed with other sun protection measures (see Directions), decreases the risk of skin cancer and early skin aging caused by the sun.

Warnings

For external use only

Do not use

on damaged or broken skin

When using this product

keep out of eyes. Rinse with water to remove.

Stop use and ask a doctor if

rash occurs

Keep out of reach of children.

If swallowed, get medical help or contact a Poison Control Center right away.

Directions

- Wear alone or under foundation.
- Shake well before use.
- Apply liberally 15 minutes before sun exposure.
- Reapply at least every 2 hours.
- Use a water resistant sunscreen if swimming or sweating.
- Sun Protection Measures. Spending time in the sun increases your risk of skin cancer and early skin aging. To decrease this risk, regularly use a sunscreen with a Broad Spectrum SPF value of 30 or higher and other sun protection measures including:
- Limit time in the sun, especially from 10 a.m.-2 p.m.
- Wear long-sleeved shirts, pants, hats and sunglasses.
- Childrenn under 6 months of age: Ask a doctor.

Other information

- Protect the product in this container from excessive heat and direct sun.
- Keep the product cool.
- After use, close the tube properly with cap.

Inactive ingredients

Water, cyclopentasiloxane, polysilicone-11, butylene glycol, cetyl PEG/PPG-10/1 dimethicone, PEG-10 dimethicone, trimethylsiloxysilicate, disteardimonium hectorite, SD alcohol 40-B, phenoxyethanol, polyglyceryl-3 polydimethyl siloxyethyl dimethicone, hydrolyzed vegetable flour, ascorbyl tetraisopalmitate, polymethylsilsesquioxane, sodium chloride, stearic acid, methyl methacrylate crosspolymer, silica, fragrance, ethylhexylglycerin, triethoxycaprylylsilane, aluminum hydroxide, laureth-12, caprylyl glycol, hexyl cinnamal benzyl salicylate, butylphenyl methylpropional, alpha-isomethyl ionone,linalool, may contain: titanium dioxide, iron oxides.